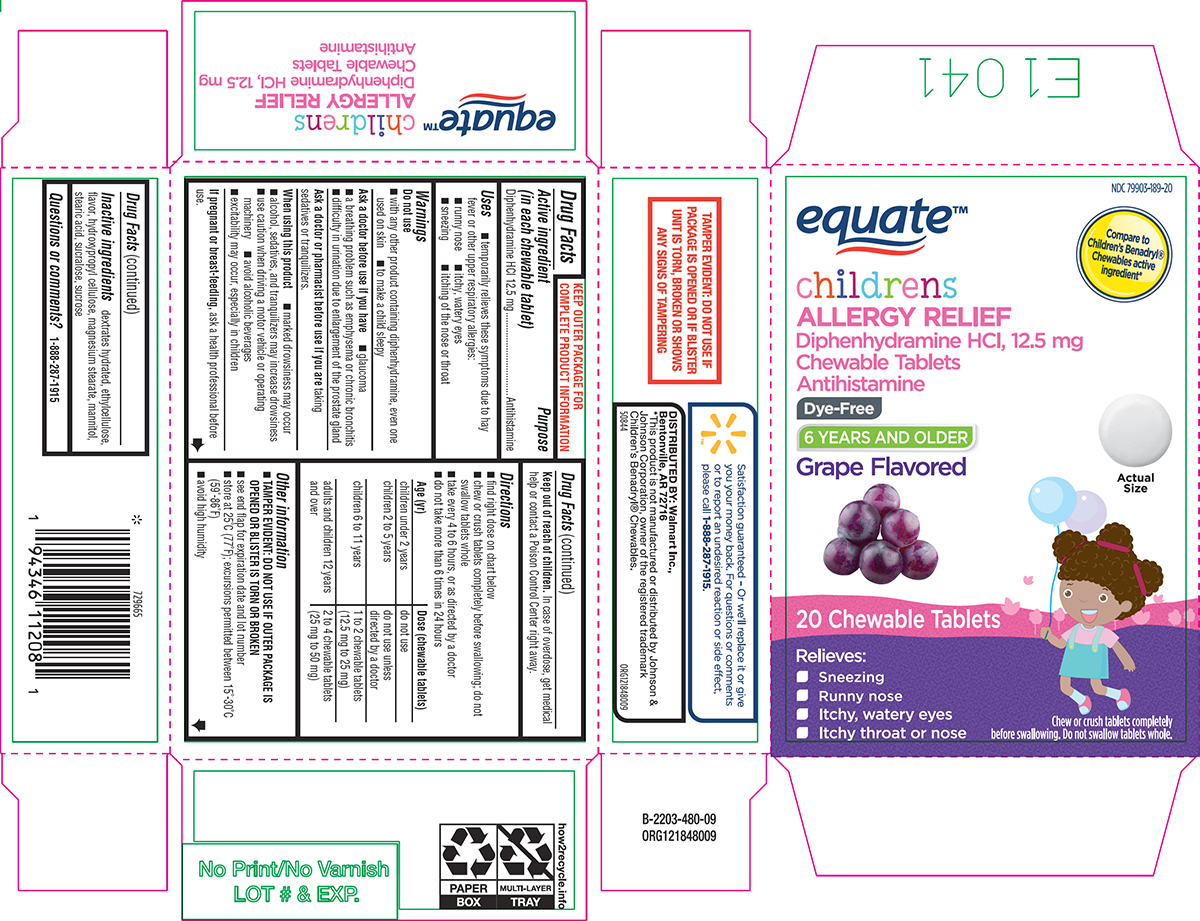 DRUG LABEL: Childrens Allergy Relief
NDC: 79903-189 | Form: TABLET, CHEWABLE
Manufacturer: WALMART INC.
Category: otc | Type: HUMAN OTC DRUG LABEL
Date: 20250607

ACTIVE INGREDIENTS: DIPHENHYDRAMINE HYDROCHLORIDE 12.5 mg/1 1
INACTIVE INGREDIENTS: DEXTROSE MONOHYDRATE; ETHYLCELLULOSE, UNSPECIFIED; HYDROXYPROPYL CELLULOSE, UNSPECIFIED; MAGNESIUM STEARATE; MANNITOL; STEARIC ACID; SUCRALOSE; SUCROSE

Equate 44-480

Active ingredient (in each chewable tablet)

Diphenhydramine HCl 12.5 mg

Purpose

Antihistamine

Uses

- temporarily relieves these symptoms due to hay fever or other upper respiratory allergies:
  - runny nose
  - itchy, watery eyes
  - sneezing
  - itching of the nose or throat

Warnings

Do not use

- with any other product containing diphenhydramine, even one used on skin
- to make a child sleepy

Ask a doctor before use if you have

- glaucoma
- a breathing problem such as emphysema or chronic bronchitis
- difficulty in urination due to enlargement of the prostate gland

Ask a doctor or pharmacist before use if you are

taking sedatives or tranquilizers.

When using this product

- marked drowsiness may occur
- alcohol, sedatives, and tranquilizers may increase drowsiness
- use caution when driving a motor vehicle or operating machinery
- avoid alcoholic beverages
- excitability may occur, especially in children

If pregnant or breast-feeding,

ask a health professional before use.

Keep out of reach of children.

In case of overdose, get medical help or contact a Poison Control Center right away.

Directions

- find right dose on chart below
- chew or crush tablets completely before swallowing; do not swallow tablets whole
- take every 4 to 6 hours, or as directed by a doctor
- do not take more than 6 times in 24 hours

Age (yr) | Dose (chewable tablets)
children under 2 years | do not use
children 2 to 5 years | do not use unless directed by a doctor
children 6 to 11 years | 1 to 2 chewable tablets (12.5 mg to 25 mg)
adults and children 12 years and over | 2 to 4 chewable tablets (25 mg to 50 mg)

Other information

- TAMPER EVIDENT: DO NOT USE IF OUTER PACKAGE IS OPENED OR BLISTER IS TORN OR BROKEN
- see end flap for expiration date and lot number
- store at 25°C (77°F); excursions permitted between 15°-30°C (59°-86°F)
- avoid high humidity

Inactive ingredients

dextrates hydrated, ethylcellulose, flavor, hydroxypropyl cellulose, magnesium stearate, mannitol, stearic acid, sucralose, sucrose

Questions or comments?

1-888-287-1915

Principal display panel

NDC 79903-189-20

equate™

Compare to
Children’s Benadryl®
Chewables active
ingredient*

childrens
ALLERGY RELIEF
Diphenhydramine HCl, 12.5 mg
Chewable Tablets
Antihistamine

Dye-Free

6 YEARS AND OLDER

Grape Flavored

Actual
Size

20 Chewable Tablets

Relieves:

• Sneezing
• Runny nose
• Itchy, watery eyes
• Itchy throat or nose

Chew or crush tablets completely
before swallowing. Do not swallow tablets whole.

TAMPER EVIDENT: DO NOT USE IF
PACKAGE IS OPENED OR IF BLISTER
UNIT IS TORN, BROKEN OR SHOWS
ANY SIGNS OF TAMPERING

Satisfaction guaranteed – Or we’ll replace it or give
you your money back. For questions or comments
or to report an undesired reaction or side effect,
please call 1-888-287-1915.

DISTRIBUTED BY: Walmart Inc.,
Bentonville, AR 72716

*This product is not manufactured or distributed by Johnson &
Johnson Corporation, owner of the registered trademark
Children’s Benadryl® Chewables.

50844 ORG121848009

Equate 44-480